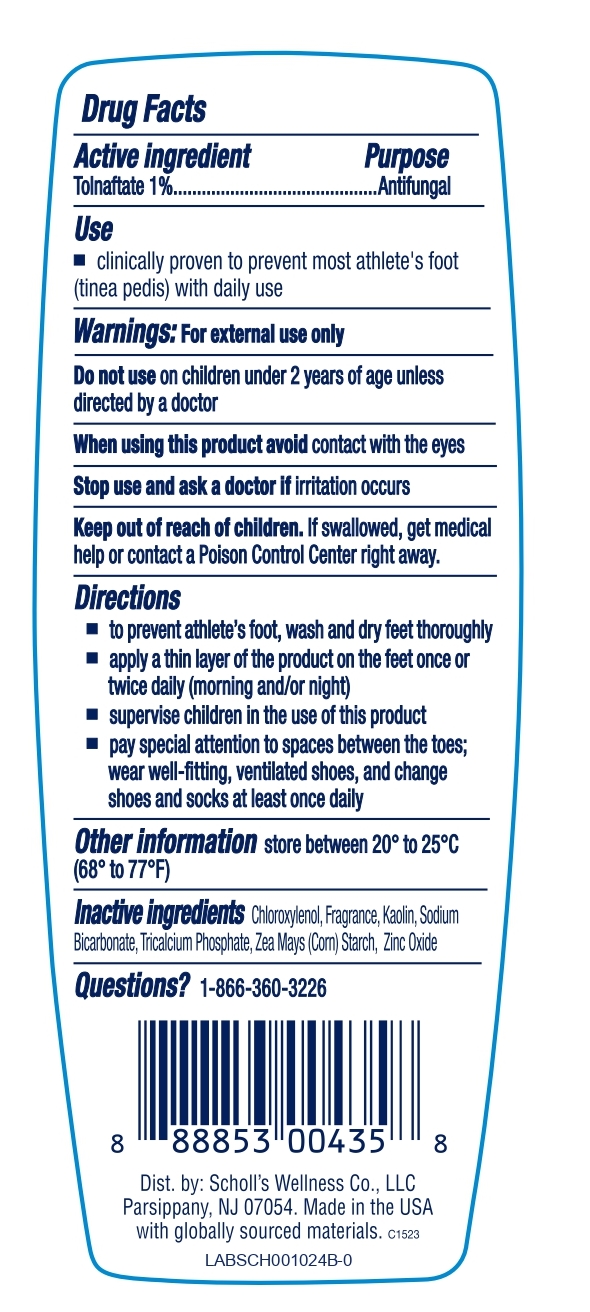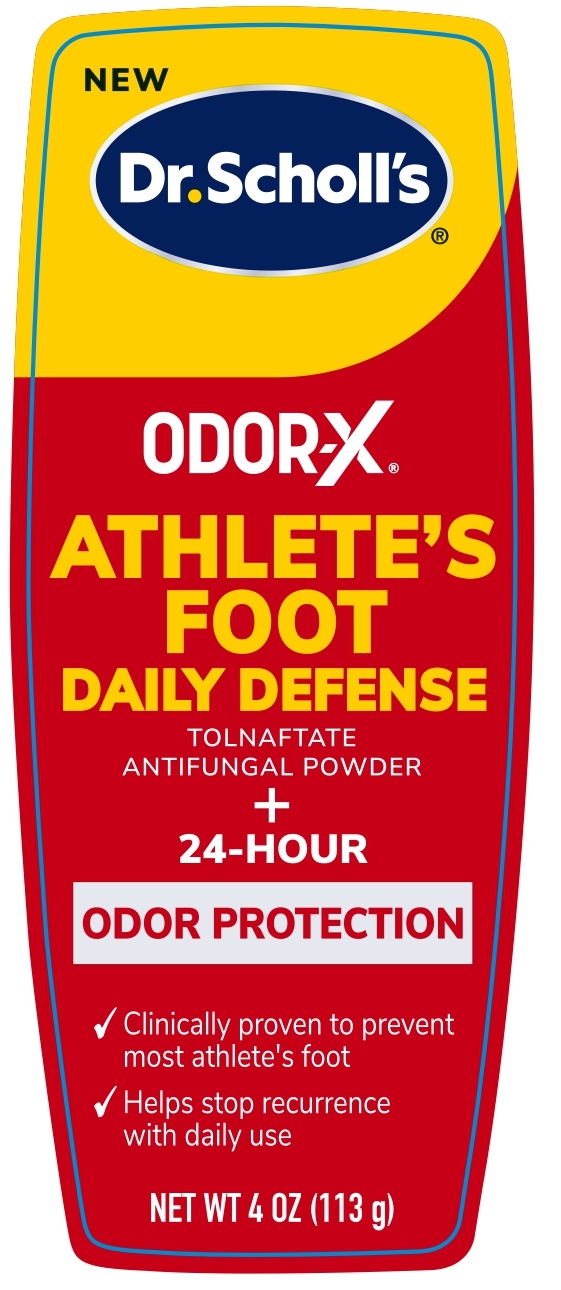 DRUG LABEL: Tolnaftate Antifungal Powder
NDC: 73469-0619 | Form: POWDER
Manufacturer: SCHOLL'S WELLNESS COMPANY LLC
Category: otc | Type: HUMAN OTC DRUG LABEL
Date: 20251206

ACTIVE INGREDIENTS: Tolnaftate 1 g/100 g
INACTIVE INGREDIENTS: CHLOROXYLENOL; KAOLIN; SODIUM BICARBONATE; TRICALCIUM PHOSPHATE; STARCH, CORN; ZINC OXIDE

Dr. Scholl's Tolnaftate Antifungal Powder

Active Ingredient

Tolnaftate 1%

Purpose

Antifungal

Use

- Clinically proven to prevent most athlete's foot (tinea pedis) with daily use

Warnings

For External use only

Do not use on children under 2 years of age unless directed by a doctor

When using this product avoid contact with the eyes

Stop use and ask a doctor if irritation occurs

Keep out of reach of children. If swallowed, get medical help or contact a Poison Control Center right away.

Directios

- to prevent athlete's foot, wash and dry feet thoroughly
- apply a thin layer of the product on the feet once or twice daily (morning and/or night)
- supervise children in the use of this product
- pay special attention to spaces between the toes; wear well-fitting, ventilated shoes, and change shoes and socks at least once daily

Other Information

Store between 20° to 25°C (68° to 77°F)

Inactive Ingredients

Chloroxylenol, Fragrance, Kaolin, Sodium Bicarbonate, Tricalcium Phosphate, Zea Mays (Corn) Starch, Zinc Oxide

Questions ?

1-866-360-3226